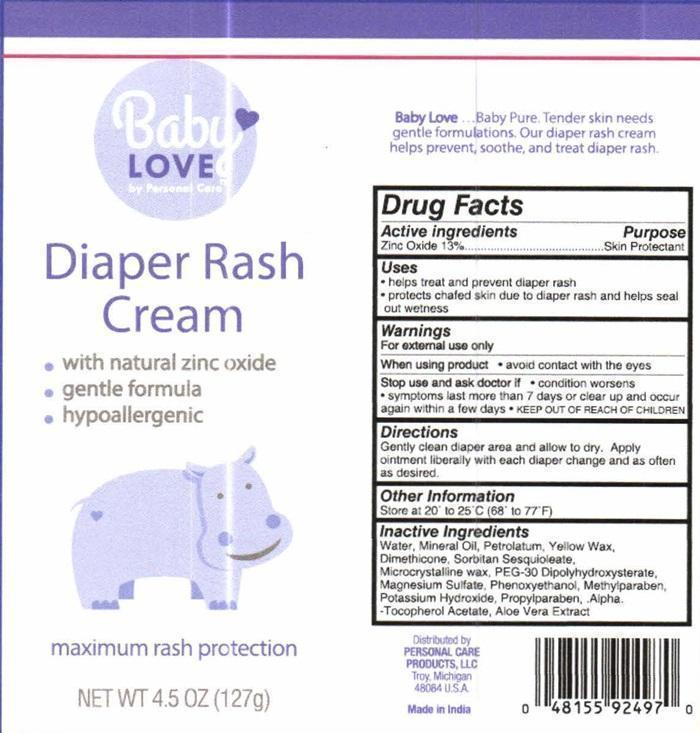 DRUG LABEL: Baby Love Diaper Rash
NDC: 29500-1497 | Form: CREAM
Manufacturer: Personal Care Products, Inc.
Category: otc | Type: HUMAN OTC DRUG LABEL
Date: 20200725

ACTIVE INGREDIENTS: ZINC OXIDE 16.51 g/127 g
INACTIVE INGREDIENTS: METHYLPARABEN; POTASSIUM HYDROXIDE; PROPYLPARABEN; .ALPHA.-TOCOPHEROL ACETATE; ALOE VERA LEAF; WATER; MINERAL OIL; PETROLATUM; YELLOW WAX; DIMETHICONE; SORBITAN SESQUIOLEATE; MICROCRYSTALLINE WAX; PEG-30 DIPOLYHYDROXYSTEARATE; MAGNESIUM SULFATE, UNSPECIFIED FORM; PHENOXYETHANOL

Drug Facts Active ingredients

Zinc Oxide 13 %

Purpose

Skin Protectant

Keep out of reach of children

Uses

- helps treat and prevent diaper rash
- protects chafed skin due to diaper rash and helps seal out wetness

Warnings

For external use only

When using product

- avoid contact with eyes

Stop use and ask a doctor if

- condition worsens
- symptoms last more than 7 days or clear up and occur again within a few days

Directions

Gently clean diaper area and allow to dry. Apply ointment liberally with each diaper change and as often as desired.

Other information

Store at 20° to 25°C (68° to 77°F)

Inactive ingredients

Water, Mineral Oil, Petrolatum, Yellow Wax, Dimethicone, Sorbitan Sesquioleate, Microcrystalline wax, Peg-30 Dipolyhydroxysterate, Magnesium Sulfate, Phenoxyethanol, Methylparaben, Potassium Hydroxide, Propylparaben, .Alpha.-Tocopherol Acetate, Aloe Vera Extract

Baby Love Diaper Rash Cream Label

Baby Love
by Personal Care ™
Diaper Rash Cream
with natural zinc oxide
gentle formula
hypoallergenic
maximum rash protection
NETWT 4.5 OZ (127 g)
Baby Love ... Baby Pure. Tender skin needs gentle formulation. Our diaper rash cream helps prevent, soothe, and treat diaper rash.
Distributed by
PERSONAL CARE PRODUCTS, LLC
Troy, Michigan 48084 U.S.A.
Made in India